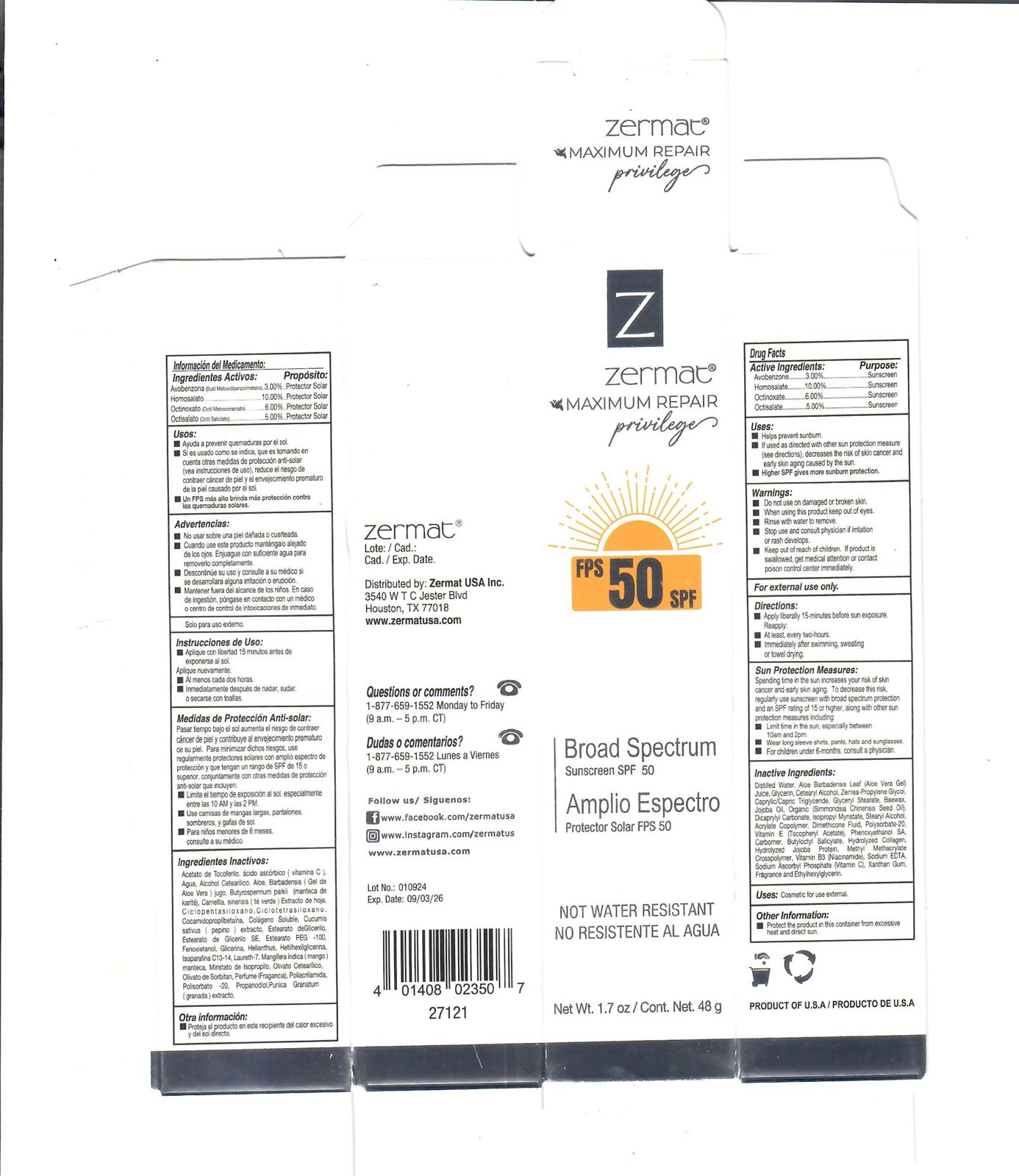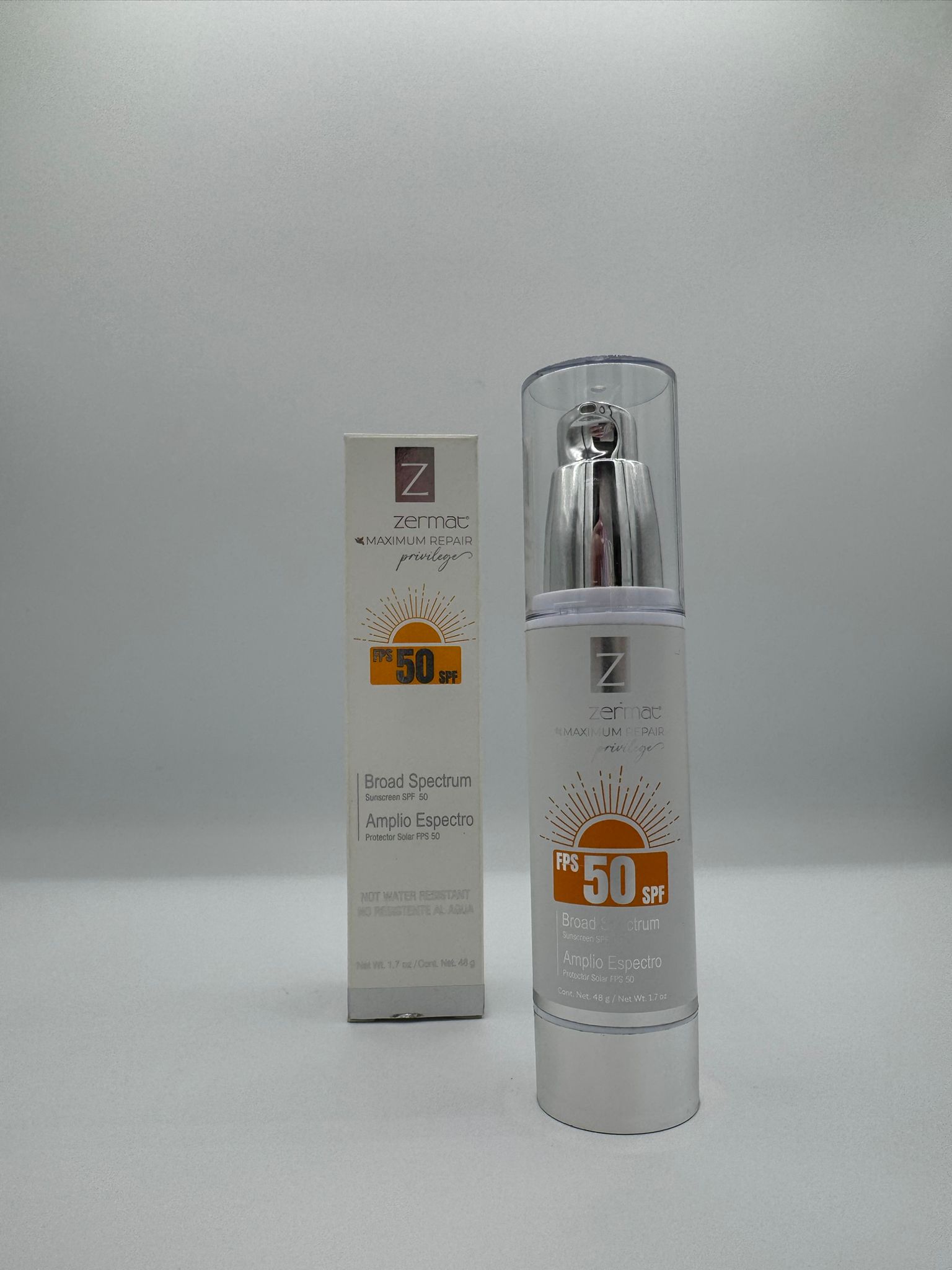 DRUG LABEL: MAXIMUM REPAIR SPF 50
NDC: 84178-008 | Form: CREAM
Manufacturer: EVI LABS
Category: otc | Type: HUMAN OTC DRUG LABEL
Date: 20260108

ACTIVE INGREDIENTS: HOMOSALATE 4.8 g/48 g; OCTISALATE 2.4 g/48 g; AVOBENZONE 1.44 g/48 g; OCTINOXATE 2.88 g/48 g
INACTIVE INGREDIENTS: YELLOW WAX 0.96 g/48 g; STEARYL ALCOHOL 0.72 g/48 g; ISOPROPYL MYRISTATE 0.96 g/48 g; GLYCERIN 1.44 g/48 g; ALOE 2.4 g/48 g; PHENOXYETHANOL 0.576 g/48 g; SODIUM ASCORBYL PHOSPHATE 0.096 g/48 g; FRAGRANCE FLORAL ORC0902236 0.48 g/48 g; CUCUMBER JUICE 0.96 g/48 g; POTASSIUM SORBATE 0.144 g/48 g; EDETATE DISODIUM 0.096 g/48 g; HYDROGENATED JOJOBA OIL, RANDOMIZED 0.96 g/48 g; MEDIUM-CHAIN TRIGLYCERIDES 0.72 g/48 g; DICAPRYLYL CARBONATE 0.01 g/48 g; CETOSTEARYL ALCOHOL 1.44 g/48 g; PROPYLENE GLYCOL 1.44 g/48 g; ETHYLHEXYLGLYCERIN 0.24 g/48 g; SODIUM BENZOATE 0.144 g/48 g; PANTHENOL 0.12 g/48 g; .ALPHA.-TOCOPHEROL ACETATE 0.48 g/48 g; NIACINAMIDE 0.24 g/48 g; COLLAGEN ALPHA-1(I) CHAIN BOVINE 0.24 g/48 g; WATER 20.39 g/48 g; DIMETHICONE 20 0.48 g/48 g; POLYSORBATE 20 0.24 g/48 g; HYDROLYZED JOJOBA ESTERS (POTASSIUM SALTS) 0.24 g/48 g; XANTHAN GUM 0.096 g/48 g; PEG-120 GLYCERYL STEARATE 1.032 g/48 g

ZERMAT_MAXIMUN REPAIR_SPF 50

Active Ingredient

- Avobenzone 3%
- Homosalate 10%
- Octinoxate 6%
- Octisalate 5%

Purpose

Sunscreen

Uses

- Helps prevent sunburn
- If used as directed with other sun protection measures (see directions), decrease the risk of skin cancer and early skin aging caused by the sun.
- Higher SPF gives more sunburn protection

Directions

- Apply liberally 15 minutes before sun exposure.
- At least, every two hours.
- Immediately after swimming, sweating, or towel drying.

Administration

For external use

Warnings

- Do not use on damaged or broken skin.
- When using this product keep out of eyes.
- Rinse with water to remove.
- Stop use and consult physician if irritation or rash develops.

Keep out of reach of children's

Keep out of children. If the product is swallowed, get medical attention or contact the poison control center immediately.

Inactive Ingredients

Water purified, Aloe Barbadensis Leaf (aloe Vera Gel) Juice, Glycerin, Cetearyl Alcohol, Zemea-Propylene Glycol, Caprylic/Capric Triglyceride, Glyceryl Stearate, Beeswax, Jojoba Oil, Organic (Simmondsia Chinensis Seed Oil), Dicaprylyl Carbonate, Isopropyl Myristate, Stearyl Alcohol, Acrylate Copolymer, Dimethicone Fluido, Polysorbate-20, Vitamin E (Tocopheryl Acetate), Phenoxyethanol SA, Carbomer, Butyloctyl Salicylate, Hydrolyzed Collagen, Hydrolyzed Jojoba Protein, Methyl Methacrylate Crosspolymer, Vitamin B3 (Niacinamide), Sodium EDTA, Sodium Ascorbyl Phosphate (Vitamin C), Xanthan Gum, Fragrance and Ehylhexylglyrecin.